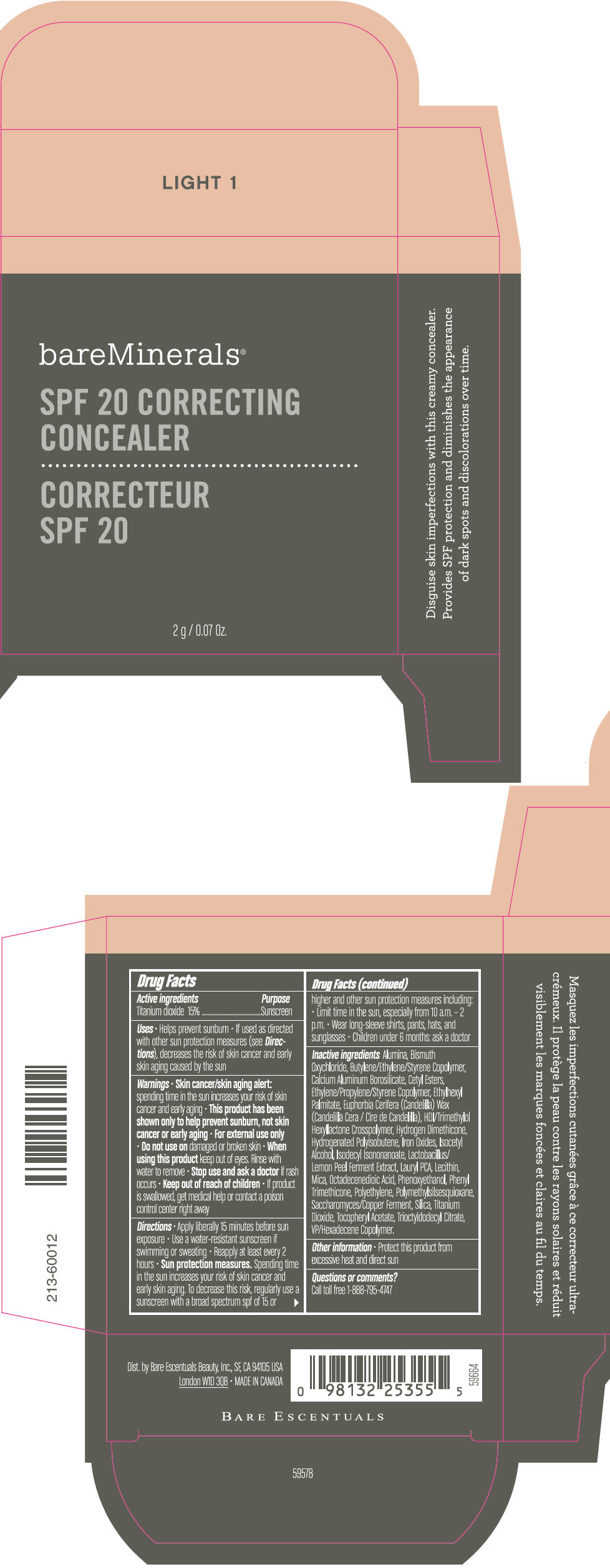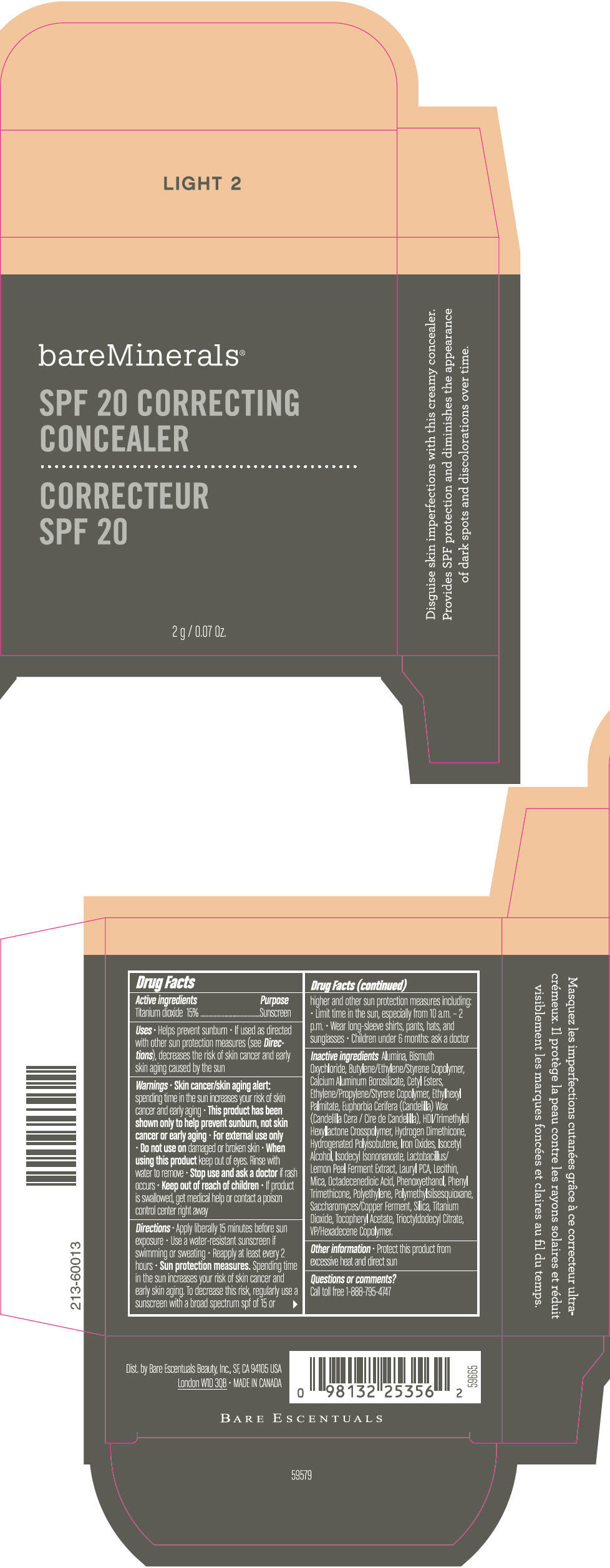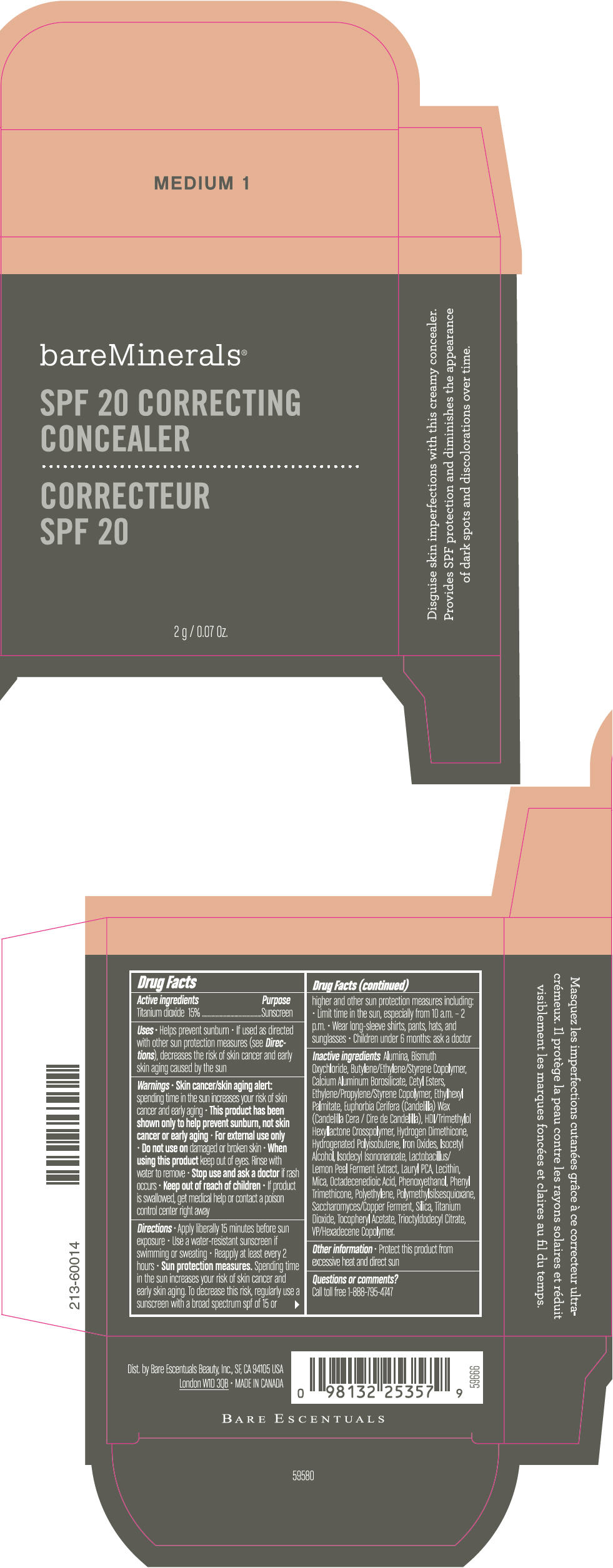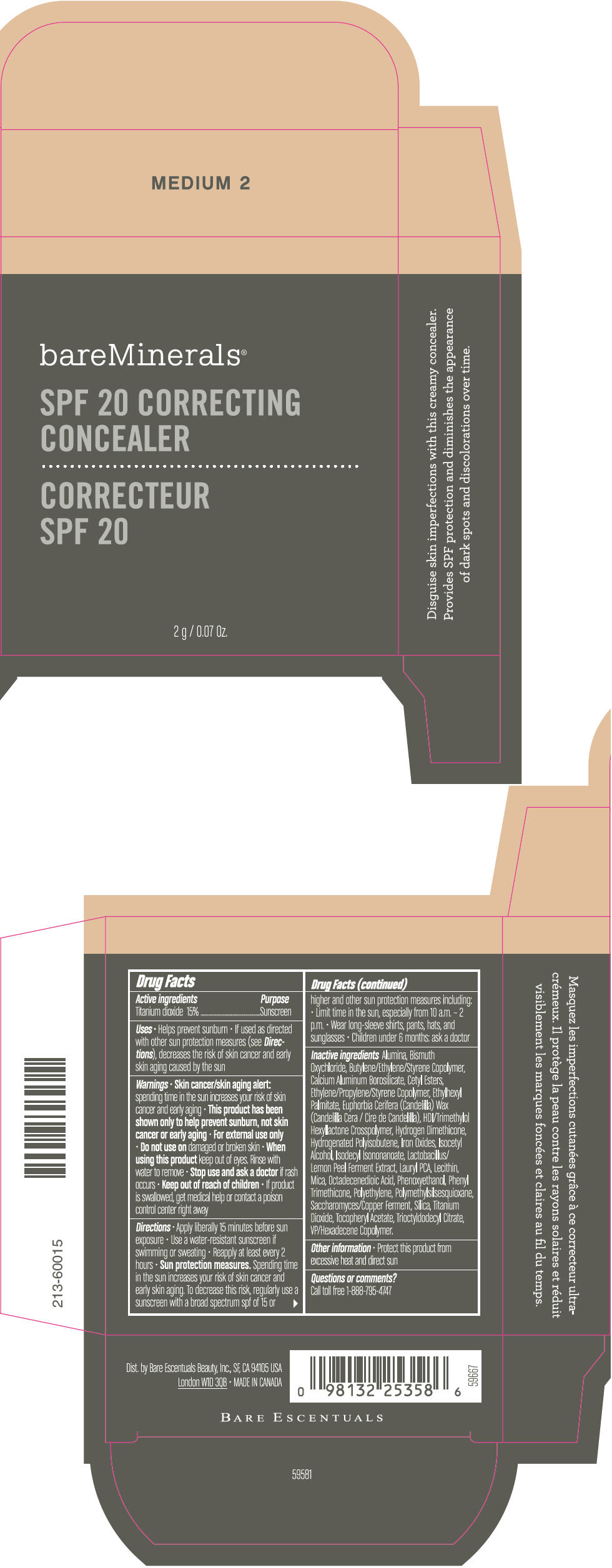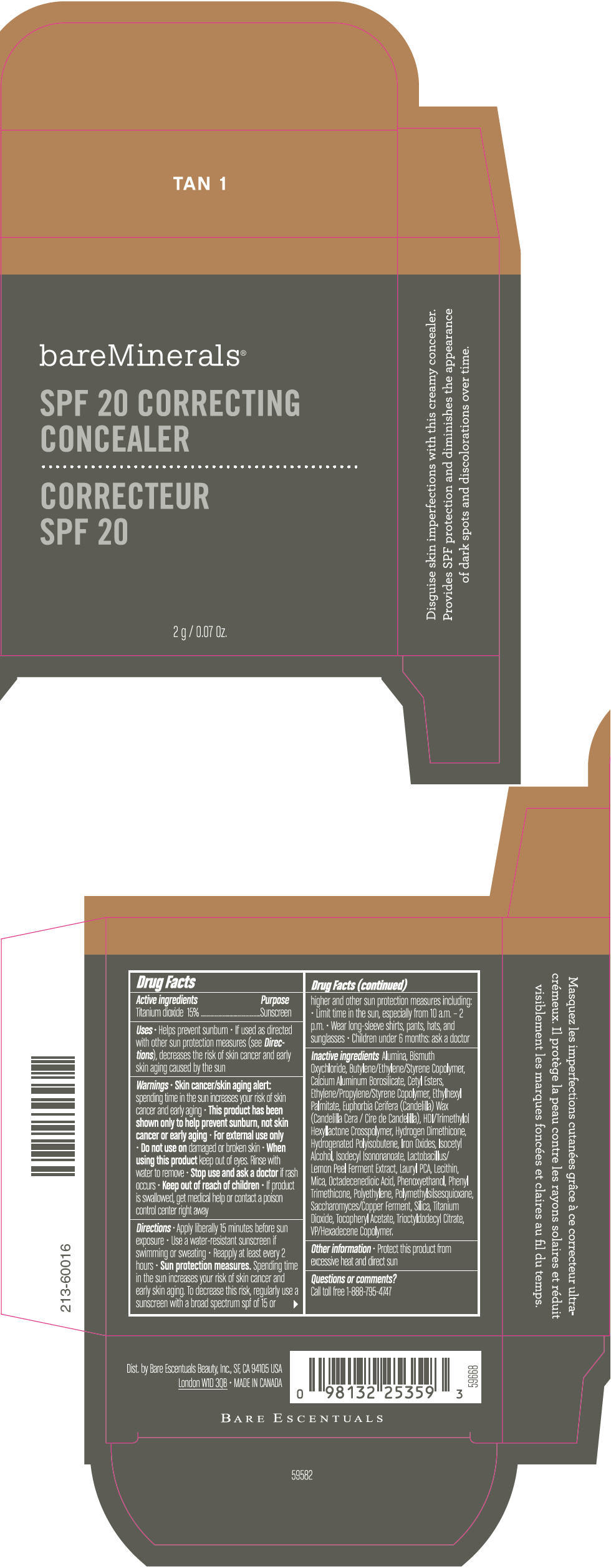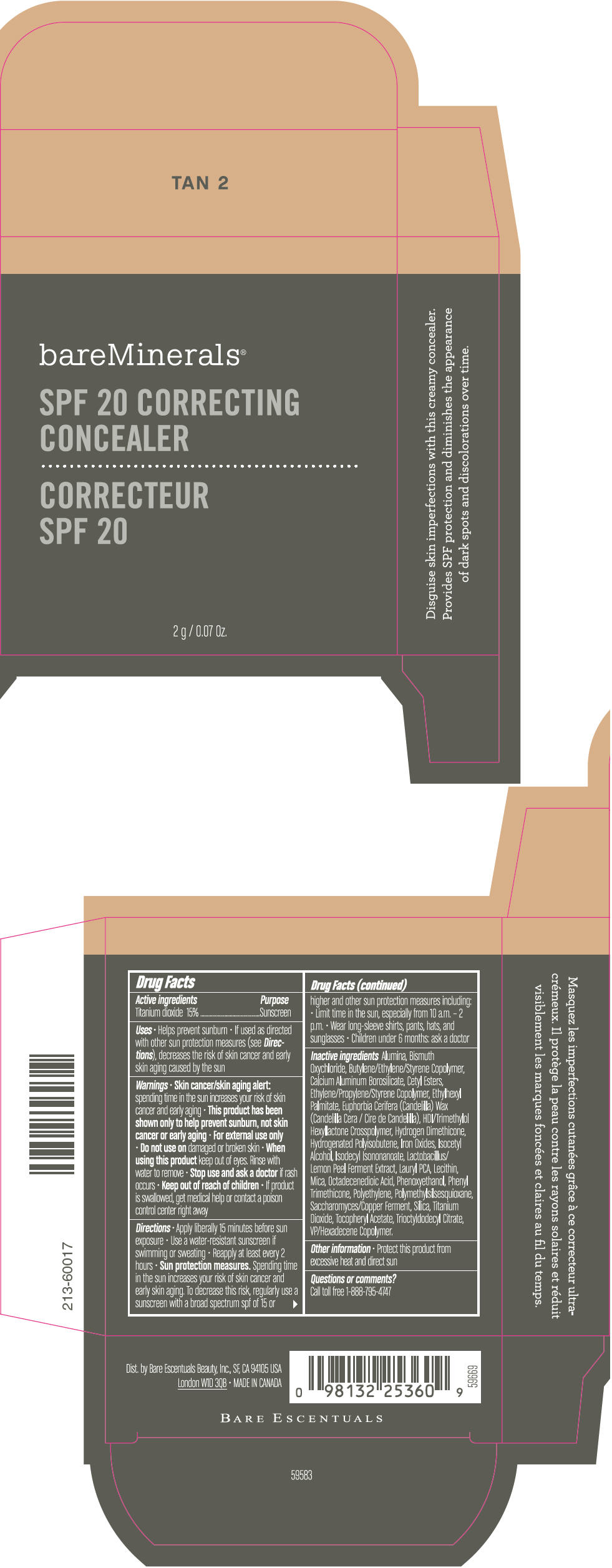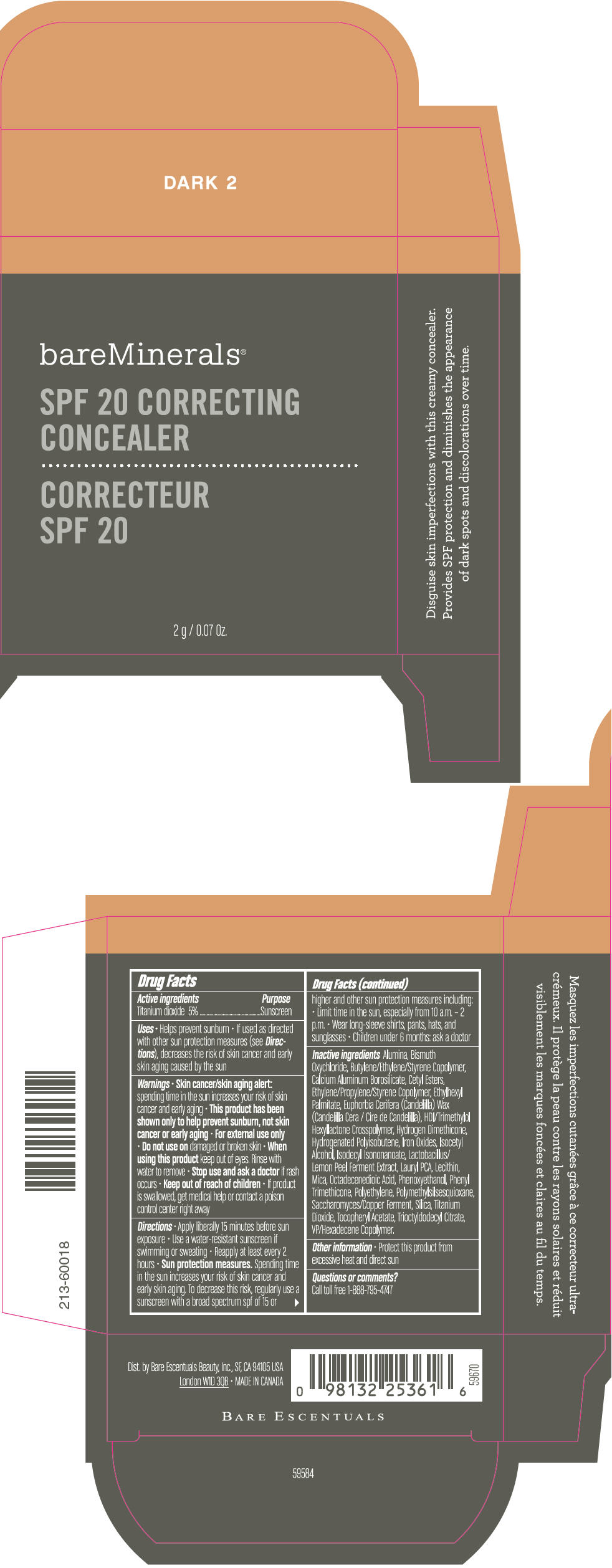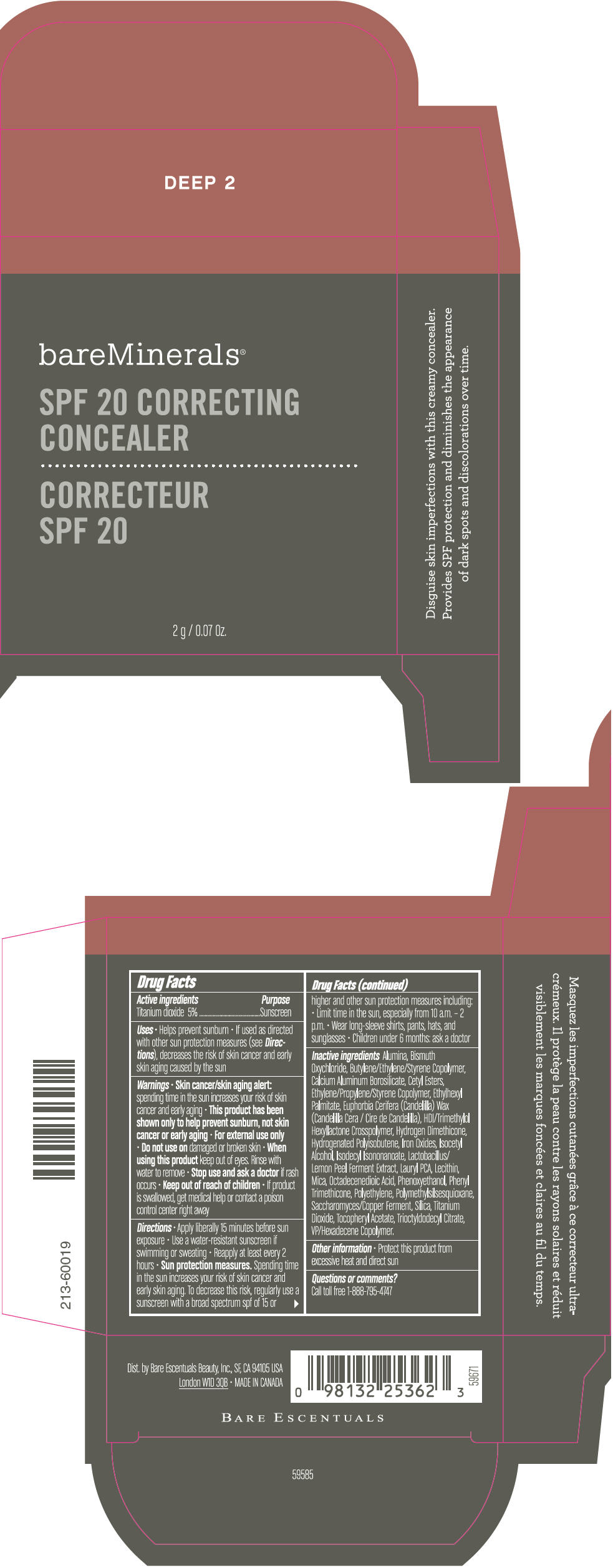 DRUG LABEL: BareMinerals 
NDC: 98132-664 | Form: CREAM
Manufacturer: Bare Escentuals Beauty Inc.
Category: otc | Type: HUMAN OTC DRUG LABEL
Date: 20120525

ACTIVE INGREDIENTS: Titanium Dioxide 0.3 g/2 g
INACTIVE INGREDIENTS: Phenyl Trimethicone; Lecithin, Soybean; .Alpha.-Tocopherol Acetate; Phenoxyethanol; Silicon Dioxide; Isocetyl Alcohol; High Density Polyethylene; Octadecenedioic Acid; Candelilla Wax; Lauryl PCA; Ethylhexyl Palmitate; Mica; Polymethylsilsesquioxane (4.5 Microns); Bismuth Oxychloride; Aluminum Oxide

BareMinerals® SPF 20 Correcting Concealer

Drug Facts

Active ingredients

Titanium dioxide 15%

Purpose

Sunscreen

Uses

- Helps prevent sunburn
- If used as directed with other sun protection measures (see Directions), decreases the risk of skin cancer and early skin aging caused by the sun

Warnings

- Skin cancer/skin aging alert: spending time in the sun increases your risk of skin cancer and early aging
- This product has been shown only to help prevent sunburn, not skin cancer or early aging
- For external use only

- Do not use on damaged or broken skin

- When using this product keep out of eyes. Rinse with water to remove

- Stop use and ask a doctor if rash occurs

- Keep out of reach of children
- If product is swallowed, get medical help or contact a poison control center right away

Directions

- Apply liberally 15 minutes before sun exposure
- Use a water-resistant sunscreen if swimming or sweating
- Reapply at least every 2 hours
- Sun protection measures. Spending time in the sun increases your risk of skin cancer and early skin aging. To decrease this risk, regularly use a sunscreen with a broad spectrum spf of 15 or higher and other sun protection measures including:
  - Limit time in the sun, especially from 10 a.m. – 2 p.m.
  - Wear long-sleeve shirts, pants, hats, and sunglasses
  - Children under 6 months: ask a doctor

Inactive ingredients

Alumina, Bismuth Oxychloride, Butylene/Ethylene/Styrene Copolymer, Calcium Aluminum Borosilicate, Cetyl Esters, Ethylene/Propylene/Styrene Copolymer, Ethylhexyl Palmitate, Euphorbia Cerifera (Candelilla) Wax (Candelilla Cera / Cire de Candelilla), HDI/Trimethylol Hexyllactone Crosspolymer, Hydrogen Dimethicone, Hydrogenated Polyisobutene, Iron Oxides, Isocetyl Alcohol, Isodecyl Isononanoate, Lactobacillus/Lemon Peel Ferment Extract, Lauryl PCA, Lecithin, Mica, Octadecenedioic Acid, Phenoxyethanol, Phenyl Trimethicone, Polyethylene, Polymethylsilsesquioxane, Saccharomyces/Copper Ferment, Silica, Titanium Dioxide, Tocopheryl Acetate, Trioctyldodecyl Citrate, VP/Hexadecene Copolymer.

Other information

- Protect this product from excessive heat and direct sun

Questions or comments?

Call toll free 1-888-795-4747

Dist. by Bare Escentuals Beauty, Inc., SF, CA 94105 USA

PRINCIPAL DISPLAY PANEL - 2 g Container Carton - LIGHT 1

bareMinerals®

SPF 20 CORRECTING
CONCEALER

2 g / 0.07 Oz.

PRINCIPAL DISPLAY PANEL - 2 g Container Carton - LIGHT 2

bareMinerals®

SPF 20 CORRECTING
CONCEALER

2 g / 0.07 Oz.

PRINCIPAL DISPLAY PANEL - 2 g Container Carton - MEDIUM 1

bareMinerals®

SPF 20 CORRECTING
CONCEALER

2 g / 0.07 Oz.

PRINCIPAL DISPLAY PANEL - 2 g Container Carton - MEDIUM 2

bareMinerals®

SPF 20 CORRECTING
CONCEALER

2 g / 0.07 Oz.

PRINCIPAL DISPLAY PANEL - 2 g Container Carton - TAN 1

bareMinerals®

SPF 20 CORRECTING
CONCEALER

2 g / 0.07 Oz.

PRINCIPAL DISPLAY PANEL - 2 g Container Carton - TAN 2

bareMinerals®

SPF 20 CORRECTING
CONCEALER

2 g / 0.07 Oz.

PRINCIPAL DISPLAY PANEL - 2 g Container Carton - DARK 2

bareMinerals®

SPF 20 CORRECTING
CONCEALER

2 g / 0.07 Oz.

PRINCIPAL DISPLAY PANEL - 2 g Container Carton - DEEP 2

bareMinerals®

SPF 20 CORRECTING
CONCEALER

2 g / 0.07 Oz.